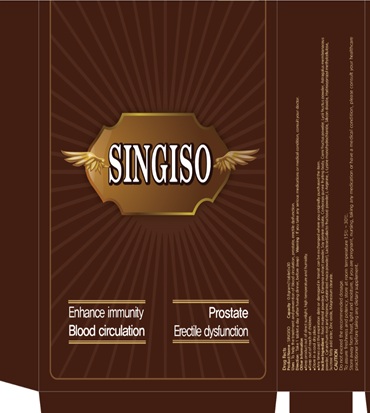 DRUG LABEL: SINGISO
NDC: 69720-1001 | Form: TABLET
Manufacturer: Sae In Dang Co., Ltd.
Category: otc | Type: HUMAN OTC DRUG LABEL
Date: 20150401

ACTIVE INGREDIENTS: ASIAN GINSENG 0.125 g/0.8 g
INACTIVE INGREDIENTS: CORNUS OFFICINALIS FRUIT; CORDYCEPS GUNNII FRUITING BODY; MAGNESIUM STEARATE; ASTRAGALUS PROPINQUUS ROOT; SOY PROTEIN; LYCIUM BARBARUM FRUIT; CYNANCHUM STAUNTONII ROOT; LEPIDIUM MEYENII WHOLE; LACTOSE; LYSINE HYDROCHLORIDE; SILICON DIOXIDE; HYPROMELLOSES; SUCROSE; ZINC OXIDE; TURNERA DIFFUSA LEAF

ACTIVE INGREDIENTS

Red ginseng 15.63%

PURPOSE

Stimulant

KEEP OUT OF REACH OF CHILDREN

USES

To help the treatment and prevention of blood circulation, prostate, erectile dysfunction.

WARNING

If you take any serious medications or medical condition, consult your doctor.

DIRECTION

Take 1 tablet a day (after having dinner, before sleep)

INACTIVE INGREDIENT

Inactive Ingredient: Food material powders (Damiana extract powder, Soy protein isolate, Cordyceps gunnii fruiting body, Corni fructus powder, Lycii fructus powder, Astragalus membranaceus powder, Cynanchum root and rhizome, Gelatinized maca powder), Lactose (Galacto fructose) powder, L-Arginine, L-Lysine monohydrochloride, Silicon dioxide, Hydroxypropyl methylcellulose, Sucrose fatty acid ester, Zinc oxide, Magnesium stearate.

OTHER INFORMATION

- Keep product out of direct sunlight, high temperature and humidity.
- Store in a cool dry place.
- Any items past the expiration date or damaged in transit can be exchanged where you originally purchased the item

SPL UNCLASSIFIED SECTION

Do not exceed the recommended dosage.

To assure freshness and potency, store at room temperature 15oC - 30oC.

Store away from heat, light and moisture, if you are pregnant, nursing, taking any medication or have a medical condition, please consult your healthcare practitioner before taking any dietary supplement.